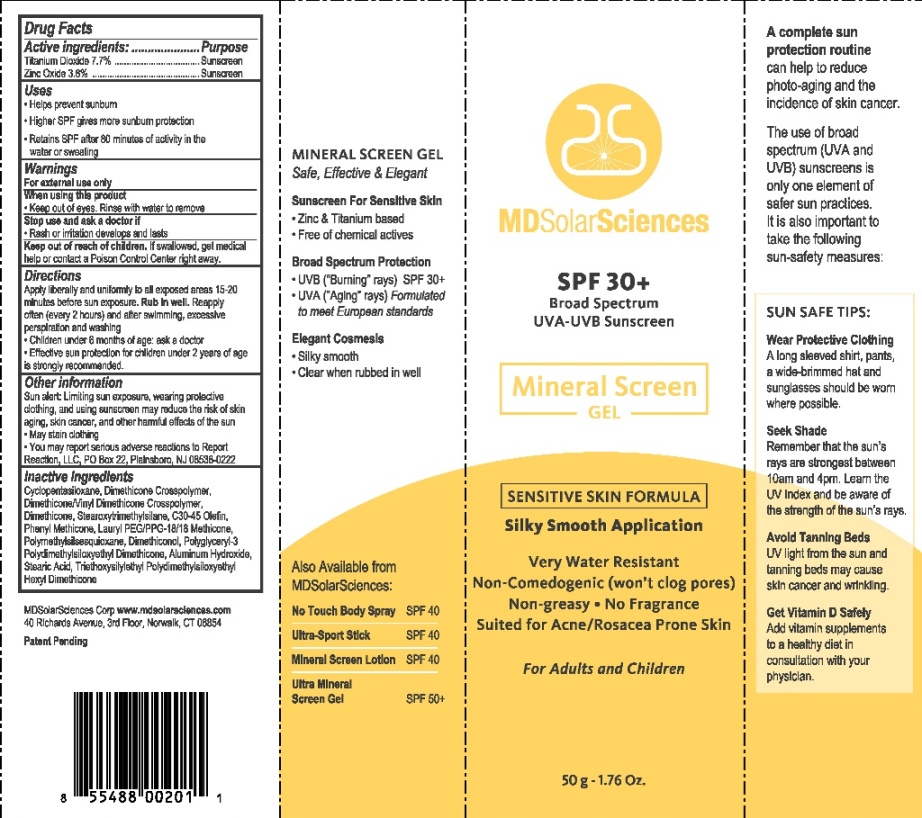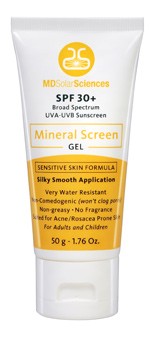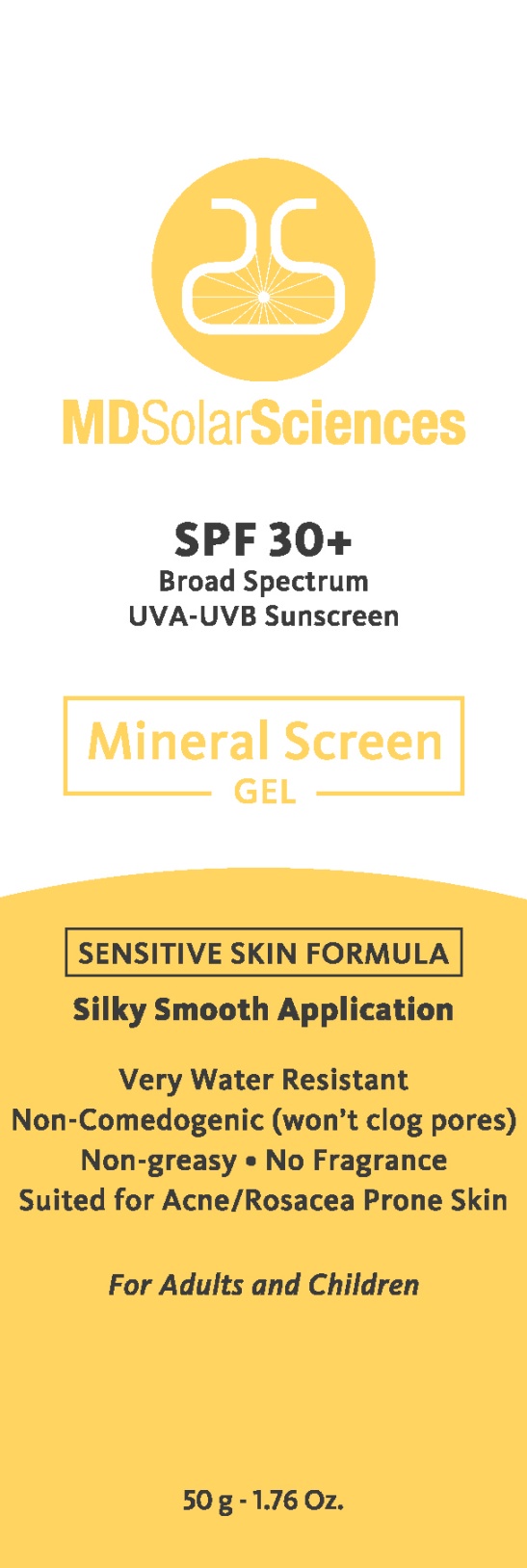 DRUG LABEL: MDSolarSciences SPF30 Plus Mineral Screen
NDC: 17452-390 | Form: GEL
Manufacturer: Ecometics, Inc
Category: otc | Type: HUMAN OTC DRUG LABEL
Date: 20101115

ACTIVE INGREDIENTS: TITANIUM DIOXIDE 7.7 g/100 g; ZINC OXIDE 3.8 g/100 g
INACTIVE INGREDIENTS: POLYMETHYLSILSESQUIOXANE (4.5 MICRONS)

Drug Facts

Active Igredients

Titanium Dioxide 7.7% .......... Sunscreen

Zinc Oxide 3.8% ................ Sunscreen

Uses

Helps prevent sunburn

Higher SPF gives more sunburn protection

Retains SPF after 80 minutes of activity in the water or sweating

Warnings

For external uses only.

When using this product
keep out of eyes. Rinse with water to remove.

Stop use and ask a doctor if
rash or irritation develops and lasts.

Keep out of reach of children.
If swallowed, get medical
help or contact a Poison ControlCenter right away

Directions

Apply liberally and uniformly to all exposed areas 15-20 minutes before sun exposure.
Rub in well. Reapply often (every 2 hours) and after swimming, excessive perspiration and washing.
Children under 6 months of age ask a doctor. Effective sun protection for children under 2 years
of age is strongly recommended.

Other Information

Sun alert: Limiting sun exposure, wearing protective
clothing, and using sunscreen may reduce the risk of skin
aging, skin cancer, and other harmful effects of the sun.
May stain clothing.
You may report serious adverse reactions to Report Reactions, LLC, PO Box 22, Plainsboro, NJ 08536-0222

Inactive Ingredients

Cyclopentasiloxane, Dimethicone Crosspolymer,
Dimethicone/Vinyl Dimethicone Crosspolymer,
Dimethicone, Stearoxytrimethylsilane, C30-45 Olefin,
Phenyl Methicone, Lauryl PEG/PPG-18/18 Methicone,
Polymethylsilsesquioxane, Dimethiconol, Polyglyceryl-3
Polydimethylsiloxyethyl Dimethicone, Aluminum Hydroxde,
Stearic Acid, Triethoxysilylethyl Polymethylsiloxyethyl
Hexyl Dimethicone.

Principle Display Panel

MDSolarSciences
SPF 30 Plus
with
Broad Spectrum
UVA-UVB Sunscreen
Mineral Screen Gel
Sensitive Skin Formula
Silky Smooth Application
Very Water Resistant
Non-Comedogenic (won't clog pores)
Non-greasy. No Fragrance
Suited for Acne/Rosacea Prone Skin
For Adults and Children
50g - 1.76 Oz

Additional Carton Labeling

MDSolarSciences Corp
40 Richards Avenue, 3rd Floor, Norwalk, CT 06854
www.mdsolarsciences.com
Patent Pending
UPC 8 55488 00201 1

MINERAL SCREEN GEL
Safe, Effective & Elegant
Suncreen For Sensitive Skin
Zinc & Titanium based
Free of chemical actives
Broad Spectrum Protection
UVB ("Burning" rays) SPF 30 Plus
UVA ("Aging" rays) Formulated
to meet European standards
Elegant Cosmesis
Silky smooth
Clear when rubbed in well

Also Available from
MDSolarSciences:
No Touch Body Spray SPF 40
Ulta-Sport Stick SPF40
Mineral Screen Lotion SPF40
Ulta Mineral
Screen Gel SPF50 Plus

A complete sun
protection routine
can help to reduce
photo-aging and the
incidence of skin cancer

The use of broad
spectum (UVA and UVB) sunscreens is
only one element of safer sun practices.
It is also important to
take the following
sun-safety measures:

SUN SAFE TIPS:
Wear Protective Clothing
A long sleeved shirt, pants,
a wide-brimmed hat and
sunglasses should be worn
where possible
Seek Shade
Remember that the sun's
rays are strongest between
10am and 4pm. Learn the
UV Index and be aware of
the strength of the sun's rays.
Avoid Tanning Beds
UV light from the sun and
tanning beds may cause
skin cancer and wrinkling
Get Vitamin D Safely
Add vitamin supplements
to a healthy diet in
consultation with your physician.